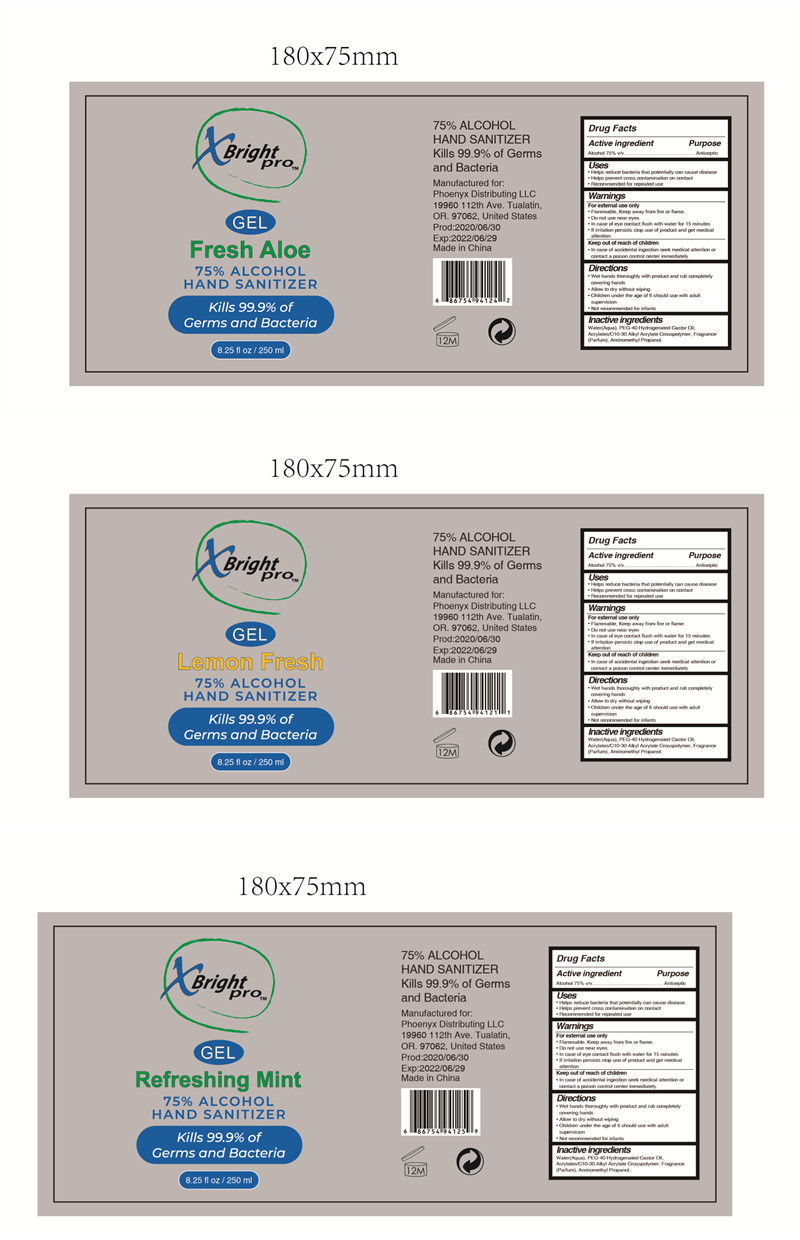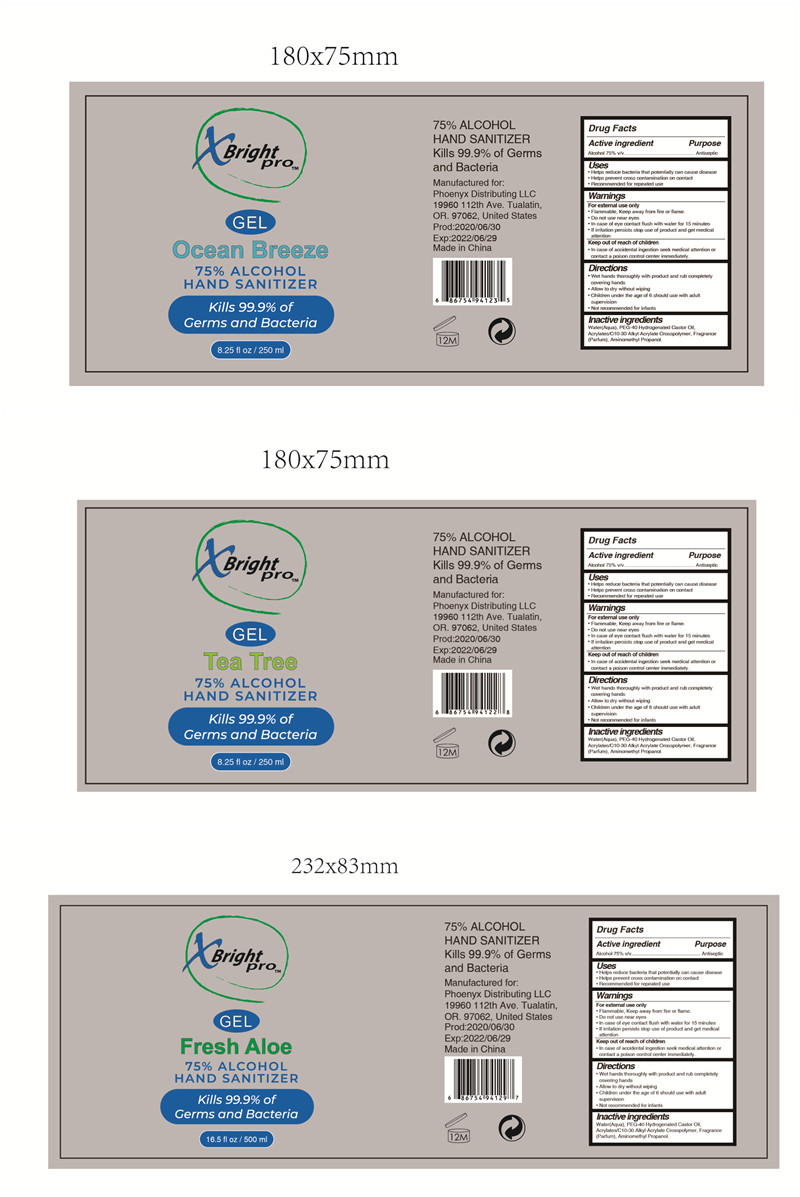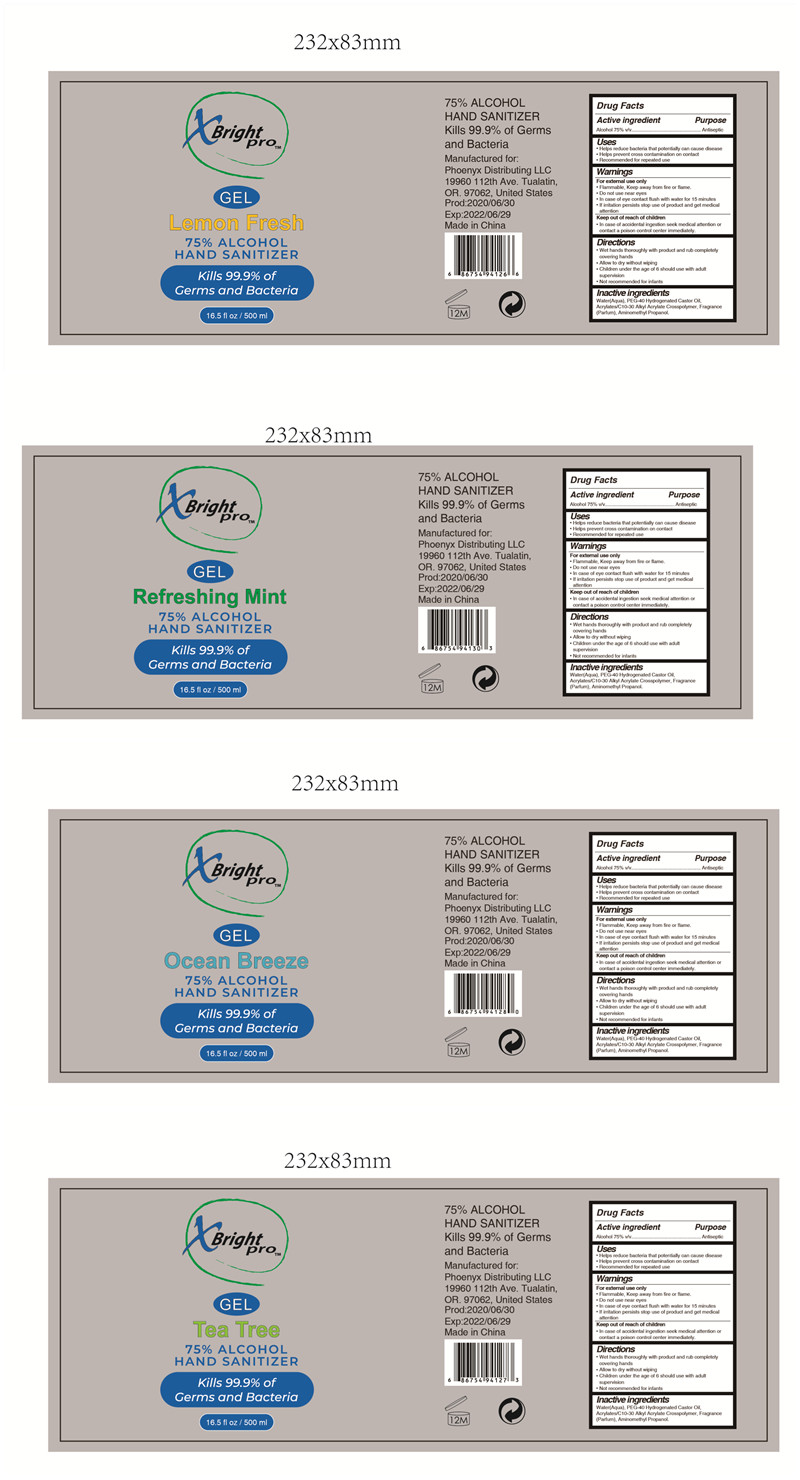 DRUG LABEL: HAND SANITIZER
NDC: 73549-007 | Form: GEL
Manufacturer: Fortress Expert Co., Ltd
Category: otc | Type: HUMAN OTC DRUG LABEL
Date: 20200624

ACTIVE INGREDIENTS: ALCOHOL 75 mL/100 mL
INACTIVE INGREDIENTS: AMINOMETHYLPROPANOL; WATER; POLYOXYL 40 HYDROGENATED CASTOR OIL; CARBOMER INTERPOLYMER TYPE A (ALLYL SUCROSE CROSSLINKED)

HAND SANITIZER

Active ingredient

Alcohol 75%v/v..

Purpose

Antiseptic

Uses

Helps reduce bacteria that potentially can cause disease

Helps prevent cross contamination on contact

Recommended for repeated use

Warnings

For external use only

Flammable, Keep away from fire or flame.

·Do not use near eyes

·In case of eye contact flush with water for 15 minutes

·If irritation persists stop use of product and get medical attention

Keep out of reach of children

In case of accidental ingestion seek medical attention or

contact a poison control center immediately.

Directions

Wet hands thoroughly with product and rub completely covering hands

·Allow to dry without wiping

·Children under the age of 6 should use with adult supervision

Not recommended for infants

Inactive ingredients

Water(Aqua) ,PEG-40 Hydrogenated Castor Oil,Acrylates/C10-30 Alkyl Acrylate Crosspolymer, Fragrance

(Parfum) , Aminomethyl Propanol.